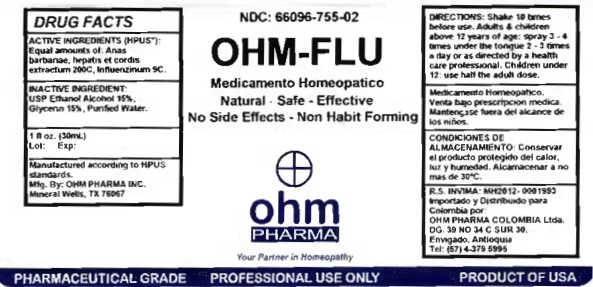 DRUG LABEL: OHM-FLU
NDC: 66096-755 | Form: SPRAY
Manufacturer: OHM PHARMA INC.
Category: homeopathic | Type: HUMAN PRESCRIPTION DRUG LABEL
Date: 20210111

ACTIVE INGREDIENTS: CAIRINA MOSCHATA HEART/LIVER AUTOLYSATE 200 [hp_C]/30 mL; INFLUENZA A VIRUS 9 [hp_C]/30 mL; INFLUENZA B VIRUS 9 [hp_C]/30 mL
INACTIVE INGREDIENTS: ALCOHOL; GLYCERIN; WATER

OHM-FLU

ACTIVE INGREDIENT

ACTIVE INGREDIENTS (HPUS*): Equal amounts of: Anas barbariae, hepatis et cordis extractum 200C, Influenzinum 9C

INDICATIONS AND USAGE

USES: Temporarily relieves relieves fever, congestion, body aches and pains. To help reduce and prevent the development of flu symptoms.**

WARNINGS

Medicamento Homeopatico.

Venta bajo prescripcion medica.

Mantengase fuera del alcance de

los niños.

KEEP OUT OF REACH OF CHILDREN

Mantengase fuera del alcance de los niños.

DOSAGE AND ADMINISTRATION

DIRECTIONS: Shake 10 times before use. Adults & children above 12 years of age: Spray 3 - 4 times under the tongue 2 - 3 times a day or as directed by a health care professional. Children under 12: use half of the adult dose.

OTHER SAFETY INFORMATION

CONDICIONES DE ALMACENAMIENTO: Conservar el producto protegido del calor, luz y humedad. Alcamacenar a no mas de 30°C.

INACTIVE INGREDIENT:

USP Ethanol Alcohol 15%,

Glycerin 15%, Purified Water

QUESTIONS

Manufactured according to HPUS

standards.

Mfg. By: OHM PHARMA INC.

Mineral Wells, TX 76067

R.S. INVIMA: MH2012-0001993

Importado y Distribuido para

Colombia por:

OHM PHARMA COLOMBIA Ltda.

DG. 39 NO 34 C SUR 30.

Tel: (57) 4-379 5995

PACKAGE LABEL

NDC: 66096-755-02

OHM-FLU

Medicamento Homeopatico

Natural - Safe - Effective

No Side Effects - Non Habit Forming

ohm PHARMA

PURPOSE

USES: Temporarily relieves relieves fever, congestion, body aches and pains. To help reduce and prevent the development of flu symptoms.**